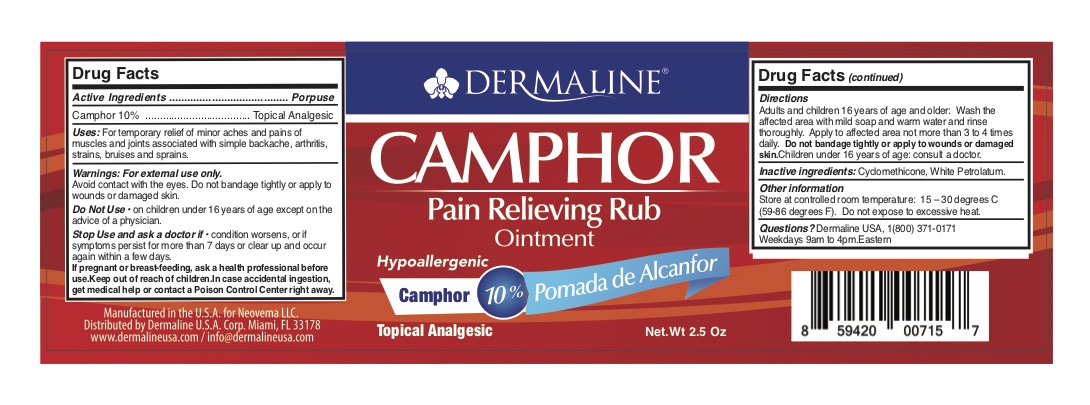 DRUG LABEL: Topical Analgesic
NDC: 82165-103 | Form: OINTMENT
Manufacturer: Dermaline USA Corp
Category: otc | Type: HUMAN OTC DRUG LABEL
Date: 20230213

ACTIVE INGREDIENTS: CAMPHOR (SYNTHETIC) 10 g/100 g
INACTIVE INGREDIENTS: WHITE PETROLATUM; CYCLOMETHICONE

Dermaline Camphor Ointment

This is a hand sanitizer manufactured according to the Temporary Policy for Preparation of Certain Alcohol-Based Hand Sanitizer Products During the Public Health Emergency (CoViD-19); Guidance for Industry.

The hand sanitizer is manufactured using only the following United States Pharmacopoeia (USP) grade ingredients in the preparation of the product (percentage in final product formulation) consistent with World Health Organization (WHO) recommendations:

1. Alcohol (ethanol) (USP or Food Chemical Codex (FCC) grade) (80%, volume/volume (v/v)) in an aqueous solution denatured according to Alcohol and Tobacco Tax and Trade Bureau regulations in 27 CFR part 20.
2. Glycerol (1.45% v/v).
3. Hydrogen peroxide (0.125% v/v).
4. Sterile distilled water or boiled cold water.

The firm does not add other active or inactive ingredients. Different or additional ingredients may impact the quality and potency of the product.

Active Ingredient(s)

Camphor 10%. Purpose: Topical Analgesic

Purpose

Topical Analgesic

Use

For temporary relief of minor aches and pains of muscles and joints associated with simple backache, arthritis, strains, bruises and sprains.

Warnings

For external use only. Flammable. Avoid contact with the eyes. Do not bandage tightly or apply to wounds or damaged skin.

Do not use

On children under 16 years of age except on the advice of a physician.

When using this product keep out of eyes, ears, and mouth. In case of contact with eyes, rinse eyes thoroughly with water.
Stop use and ask a doctor if irritation or rash occurs. These may be signs of a serious condition.
Keep out of reach of children. If swallowed, get medical help or contact a Poison Control Center right away.

Stop use and ask a doctor if condition worsens, or if symtpoms persist for more than 7 days or clear up and occur again within a few days.

Keep out of reach of children. If swallowed, get medical help or contact a Poison Control Center right away.

Directions

Adults and children 16 years of age and older. Wash the affected area with mild soap and warm water and rinse thorougly. Apply to affected area not more than 3 to 4 times a day.

Other information

- Store between 15-30C (59-86F)
- Do not expose to excessive heat

Inactive ingredients

cyclomethicone, white petrolatum

Package Label - Principal Display Panel

70g NDC: 82165-103-02